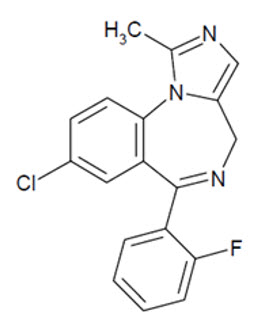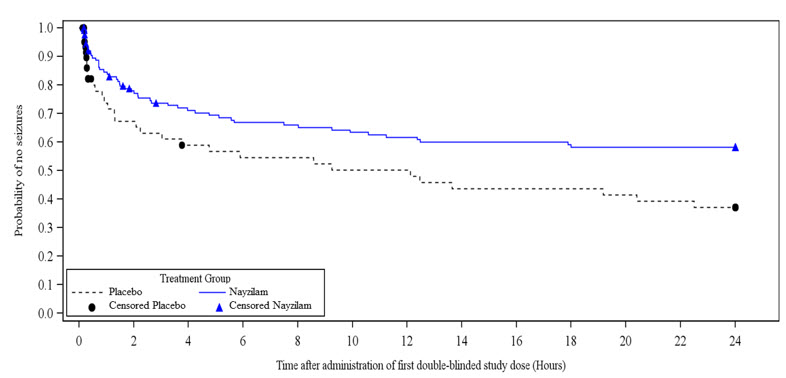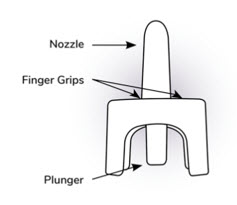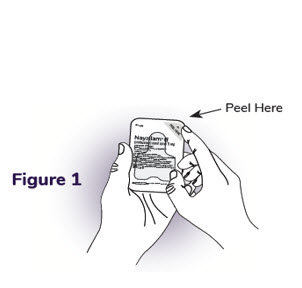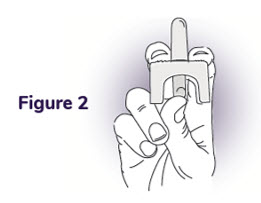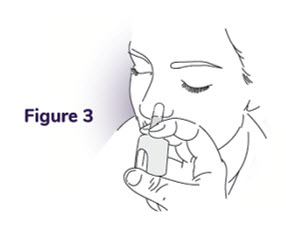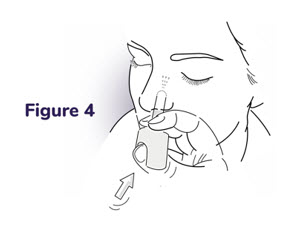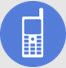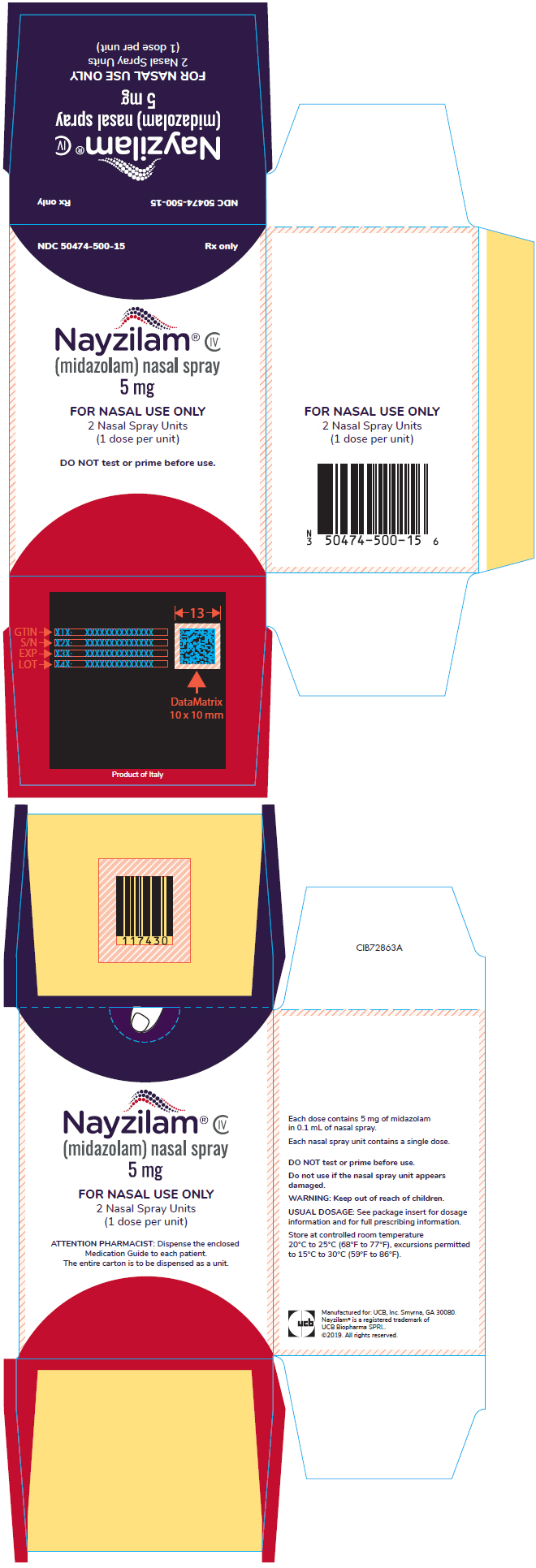 DRUG LABEL: Nayzilam
NDC: 50474-500 | Form: SPRAY
Manufacturer: UCB, Inc.
Category: prescription | Type: HUMAN PRESCRIPTION DRUG LABEL
Date: 20230119
DEA Schedule: CIV

ACTIVE INGREDIENTS: midazolam 5 mg/0.1 mL
INACTIVE INGREDIENTS: PEG-6 methyl ether; polyethylene glycol 400; propylene glycol; water; alcohol

HIGHLIGHTS OF PRESCRIBING INFORMATION

These highlights do not include all the information needed to use NAYZILAM® safely and effectively. See full prescribing information for NAYZILAM®.
NAYZILAM® (midazolam) nasal spray, CIV
Initial U.S. Approval: 1985

WARNING: RISKS FROM CONCOMITANT USE WITH OPIOIDS; ABUSE, MISUSE, AND ADDICTION; and DEPENDENCE AND WITHDRAWAL REACTIONS

See full prescribing information for complete boxed warning.

- Concomitant use of benzodiazepines and opioids may result in profound sedation, respiratory depression, coma, and death (5.1, 7.2)
- The use of benzodiazepines, including NAYZILAM, exposes users to risks of abuse, misuse, and addiction, which can lead to overdose or death. Before prescribing NAYZILAM and throughout treatment, assess each patient's risk for abuse, misuse, and addiction (5.2).
- Although NAYZILAM is indicated only for intermittent use (1, 2), if used more frequently than recommended, abrupt discontinuation or rapid dosage reduction of NAYZILAM may precipitate acute withdrawal reactions, which can be life-threatening. For patients using NAYZILAM more frequently than recommended, to reduce the risk of withdrawal reactions, use a gradual taper to discontinue NAYZILAM (5.3).

RECENT MAJOR CHANGES

Warnings and Precautions (5.9) | 1/2023

1 INDICATIONS AND USAGE

NAYZILAM is a benzodiazepine indicated for the acute treatment of intermittent, stereotypic episodes of frequent seizure activity (i.e., seizure clusters, acute repetitive seizures) that are distinct from a patient's usual seizure pattern in patients with epilepsy 12 years of age and older. (1)

2 DOSAGE AND ADMINISTRATION

Administer NAYZILAM by the nasal route only. (2.2)

Initial Dose: Administer one spray (5 mg dose) into one nostril. (2.2)

Second Dose: One additional spray (5 mg dose) into the opposite nostril may be administered after 10 minutes if the patient has not responded to the initial dose. (2.2)

Maximum Dosage and Treatment Frequency: Do not use more than 2 doses of NAYZILAM to treat a seizure cluster. It is recommended that NAYZILAM be used to treat no more than one episode every three days and treat no more than five episodes per month. (2.2)

3 DOSAGE FORMS AND STRENGTHS

Single-dose nasal spray unit containing 5 mg midazolam per 0.1 mL solution. (3)

4 CONTRAINDICATIONS

- Patients with hypersensitivity to midazolam (4)
- Patients with acute narrow-angle glaucoma (4)

5 WARNINGS AND PRECAUTIONS

- CNS Depression From Concomitant Use With Other CNS Depressants or Moderate or Strong CYP3A4 Inhibitors: May cause an increased CNS-depressant effect when used with alcohol or other CNS depressants. Concomitant use with moderate or strong CYP3A4 inhibitors may result in prolonged sedation because of a decrease in plasma clearance of midazolam. (5.5, 7.3)
- Suicidal Behavior and Ideation: Antiepileptic drugs increase the risk of suicidal ideation and behavior. (5.6)
- Impaired Cognitive Function: Midazolam is associated with a high incidence of partial or complete impairment of recall for the next several hours. (5.7)
- Glaucoma: NAYZILAM can increase intraocular pressure in patients with glaucoma. Patients with open-angle glaucoma may need to have their ophthalmologic status evaluated following treatment with NAYZILAM. (5.8)
- Neonatal Sedation and Withdrawal Syndrome: NAYZILAM use during pregnancy can result in neonatal sedation and/or neonatal withdrawal. (5.9, 8.1)

6 ADVERSE REACTIONS

The most common adverse reactions (≥5% in any NAYZILAM treatment group) were somnolence, headache, nasal discomfort, throat irritation, and rhinorrhea (6.1)

To report SUSPECTED ADVERSE REACTIONS, contact UCB, Inc. at 1-844-599-2273 or FDA at 1-800-FDA-1088 or www.fda.gov/medwatch.

7 DRUG INTERACTIONS

- CYP3A4 Inhibitors: Avoid co-administration of NAYZILAM with moderate or strong CYP3A4 inhibitors. NAYZILAM should be used with caution when co-administered with mild CYP3A4 inhibitors. (7.1)
- Opioids: Risk of respiratory depression is increased. (7.2)
- Other CNS Depressants: May increase the risks of hypoventilation, airway obstruction, desaturation, or apnea and may contribute to profound and/or prolonged drug effect. (7.3)

8 USE IN SPECIFIC POPULATIONS

- Pregnancy: Based on animal data, may cause fetal harm. (8.1)
- Lactation: Midazolam is excreted in human milk. Caution should be exercised when NAYZILAM is administered to a nursing woman. (8.2)
- Renal Impairment: Patients with renal impairment may have longer elimination half-lives for midazolam and its metabolites which may result in prolonged exposure. (8.6)

FULL PRESCRIBING INFORMATION

WARNING: RISKS FROM CONCOMITANT USE WITH OPIOIDS; ABUSE, MISUSE, AND ADDICTION; and DEPENDENCE AND WITHDRAWAL REACTIONS

- Concomitant use of benzodiazepines and opioids may result in profound sedation, respiratory depression, coma, and death. Reserve concomitant prescribing of these drugs for patients for whom alternative treatment options are inadequate. Limit dosages and durations to the minimum required. Follow patients for signs and symptoms of respiratory depression and sedation [see Warnings and Precautions (5.1) and Drug Interactions (7.2)].
- The use of benzodiazepines, including NAYZILAM, exposes users to risks of abuse, misuse, and addiction, which can lead to overdose or death. Abuse and misuse of benzodiazepines commonly involve concomitant use of other medications, alcohol, and/or illicit substances, which is associated with an increased frequency of serious adverse outcomes. Before prescribing NAYZILAM and throughout treatment, assess each patient's risk for abuse, misuse, and addiction [see Warnings and Precautions (5.2)].
- The continued use of benzodiazepines may lead to clinically significant physical dependence. The risks of dependence and withdrawal increase with longer treatment duration and higher daily dose. Although NAYZILAM is indicated only for intermittent use [see Indications and Usage (1) and Dosage and Administration (2)], if used more frequently than recommended abrupt discontinuation or rapid dosage reduction of NAYZILAM may precipitate acute withdrawal reactions, which can be life-threatening. For patients using NAYZILAM more frequently than recommended, to reduce the risk of withdrawal reactions, use a gradual taper to discontinue NAYZILAM [see Warnings and Precautions (5.3)].

1 INDICATIONS AND USAGE

NAYZILAM is indicated for the acute treatment of intermittent, stereotypic episodes of frequent seizure activity (i.e., seizure clusters, acute repetitive seizures) that are distinct from a patient's usual seizure pattern in patients with epilepsy 12 years of age and older.

2 DOSAGE AND ADMINISTRATION

2.1 Instructions Prior to Dosing

NAYZILAM prescribers should consider the following prior to initiation of treatment:

For patients at increased risk of respiratory depression from benzodiazepines, administration of NAYZILAM under healthcare professional supervision should be considered prior to treatment with NAYZILAM; this administration may be performed in the absence of a seizure episode [see Warnings and Precautions (5.4)].

Prior to treatment, the healthcare professional should instruct the individual administering NAYZILAM on how to identify seizure clusters and use the product appropriately [see Patient Counseling Information: Administration Information (17)]. Patients and caregivers should be counseled to read carefully the "Instructions for Use" for complete directions on how to properly administer NAYZILAM.

2.2 Dosage Information

Administer NAYZILAM by the nasal route only.

Initial Dose: Administer one spray (5 mg dose) into one nostril.

Second Dose (if needed): One additional spray (5 mg dose) into the opposite nostril may be administered after 10 minutes if the patient has not responded to the initial dose.

A second dose of NAYZILAM should not be administered if the patient has trouble breathing or if there is excessive sedation that is uncharacteristic of the patient during a seizure cluster episode [see Warnings and Precautions (5.4)].

Maximum Dosage and Treatment Frequency: Do not use more than 2 doses of NAYZILAM to treat a single episode.

It is recommended that NAYZILAM be used to treat no more than one episode every three days and no more than 5 episodes per month [see Drug Abuse and Dependence (9.4)].

3 DOSAGE FORMS AND STRENGTHS

NAYZILAM is supplied as a single-dose nasal spray unit containing 5 mg of midazolam in 0.1 mL solution.

4 CONTRAINDICATIONS

NAYZILAM is contraindicated in patients with:

- Known hypersensitivity to midazolam.
- Acute narrow-angle glaucoma [see Warnings and Precautions (5.8)].

5 WARNINGS AND PRECAUTIONS

5.1 Risks from Concomitant Use with Opioids

Concomitant use of benzodiazepines, including NAYZILAM, and opioids may result in profound sedation, respiratory depression, coma, and death. Because of these risks, reserve concomitant prescribing of benzodiazepines and opioids for patients for whom alternative treatment options are inadequate.

Observational studies have demonstrated that concomitant use of opioid analgesics and benzodiazepines increases the risk of drug-related mortality compared to use of opioids alone. If a decision is made to prescribe NAYZILAM concomitantly with opioids, prescribe the lowest effective dosages and minimum durations of concomitant use, and follow patients closely for signs and symptoms of respiratory depression and sedation. Advise both patients and caregivers about the risks of respiratory depression and sedation when NAYZILAM is used with opioids [see Drug Interactions (7.2)].

5.2 Abuse, Misuse, and Addiction

The use of benzodiazepines, including NAYZILAM, exposes users to the risks of abuse, misuse, and addiction, which can lead to overdose or death. Abuse and misuse of benzodiazepines often (but not always) involve the use of doses greater than the maximum recommended dosage and commonly involve concomitant use of other medications, alcohol, and/or illicit substances, which is associated with an increased frequency of serious adverse outcomes, including respiratory depression, overdose, or death [see Drug Abuse and Dependence (9.2)].

Before prescribing NAYZILAM and throughout treatment, assess each patient's risk for abuse, misuse, and addiction. Use of NAYZILAM, particularly in patients at elevated risk, necessitates counseling about the risks and proper use of NAYZILAM along with monitoring for signs and symptoms of abuse, misuse, and addiction. Do not exceed the recommended dosing frequency; avoid or minimize concomitant use of CNS depressants and other substances associated with abuse, misuse, and addiction (e.g., opioid analgesics, stimulants); and advise patients on the proper disposal of unused drug. If a substance use disorder is suspected, evaluate the patient and institute (or refer them for) early treatment, as appropriate.

5.3 Dependence and Withdrawal Reactions After Use of NAYZILAM More Frequently Than Recommended

For patients using NAYZILAM more frequently than recommended, to reduce the risk of withdrawal reactions, use a gradual taper to discontinue NAYZILAM (a patient-specific plan should be used to taper the dose). Patients at an increased risk of withdrawal adverse reactions after benzodiazepine discontinuation or rapid dosage reduction include those who take higher dosages, and those who have had longer durations of use.

Acute Withdrawal Reactions

The continued use of benzodiazepines may lead to clinically significant physical dependence. Although NAYZILAM is indicated only for intermittent use [see Indications and Usage (1) and Dosage and Administration (2)], if used more frequently than recommended, abrupt discontinuation or rapid dosage reduction of NAYZILAM, or administration of flumazenil (a benzodiazepine antagonist) may precipitate acute withdrawal reactions, which can be life-threatening (e.g., seizures) [see Drug Abuse and Dependence (9.3)].

Protracted Withdrawal Syndrome

In some cases, benzodiazepine users have developed a protracted withdrawal syndrome with withdrawal symptoms lasting weeks to more than 12 months [see Drug Abuse and Dependence (9.3)].

5.4 Risks of Cardiorespiratory Adverse Reactions

Serious cardiorespiratory adverse reactions have occurred after administration of midazolam. These have included respiratory depression, airway obstruction, oxygen desaturation, apnea, respiratory arrest and/or cardiac arrest, sometimes resulting in death or permanent neurologic injury. There have also been rare reports of hypotensive episodes requiring treatment during or after diagnostic or surgical manipulations, particularly in patients with hemodynamic instability. Hypotension occurs more frequently in patients premedicated with a narcotic. The danger of hypoventilation, airway obstruction, or apnea is greater in elderly patients and those with chronic disease states or decreased pulmonary reserve [see Use in Specific Populations (8.5)]; patients with chronic obstructive pulmonary disease are highly sensitive to the respiratory depressant effect of midazolam.

Respiratory depression was observed with the administration of NAYZILAM during clinical trials [see Adverse Reactions (6.1)]. Cardiac or respiratory arrest caused by NAYZILAM was not reported during clinical trials.

5.5 Central Nervous System Depression from Concomitant Use with Other Central Nervous System Depressants, or Moderate or Strong CYP3A4 Inhibitors

Drug products containing midazolam, including NAYZILAM, have a central nervous system (CNS) depressant effect.

Risks from Concomitant Use with Other CNS Depressants

The potential for an increased CNS-depressant effect from concomitant use with alcohol or other CNS depressants (e.g., opioids) must be considered by the prescribing physician, and appropriate recommendations made to the patient and/or caregiver [see Warnings and Precautions (5.1) and Drug Abuse and Dependence (9.3)].

Concomitant use of barbiturates, alcohol, or other CNS depressants may increase the risk of hypoventilation, airway obstruction, desaturation, or apnea and may contribute to profound and/or prolonged drug effect [see Drug Interactions (7.3)].

Risks from Concomitant Use with Moderate or Strong CYP3A4 Inhibitors

There is a potential for prolonged sedation from concomitant use with moderate or strong CYP3A4 enzyme inhibitors because of much higher midazolam exposures [see Drug Interactions (7.2) and Clinical Pharmacology (12.2)].

5.6 Suicidal Behavior and Ideation

Antiepileptic drugs (AEDs), including NAYZILAM, increase the risk of suicidal thoughts or behavior in patients taking these drugs for any indication. Patients treated with any AED for any indication should be monitored for the emergence or worsening of depression, suicidal thoughts or behavior, and/or any unusual changes in mood or behavior.

Pooled analyses of 199 placebo-controlled clinical trials (mono- and adjunctive therapy) of 11 different AEDs showed that patients randomized to one of the AEDs had approximately twice the risk (adjusted Relative Risk 1.8, 95% CI:1.2, 2.7) of suicidal thinking or behavior compared to patients randomized to placebo. In these trials, which had a median treatment duration of 12 weeks, the estimated incidence rate of suicidal behavior or ideation among 27,863 AED-treated patients was 0.43%, compared to 0.24% among 16,029 placebo-treated patients, representing an increase of approximately one case of suicidal thinking or behavior for every 530 patients treated. There were four suicides in drug-treated patients in the trials and none in placebo-treated patients, but the number is too small to allow any conclusion about drug effect on suicide.

The increased risk of suicidal thoughts or behavior with AEDs was observed as early as one week after starting drug treatment with AEDs and persisted for the duration of treatment assessed. Because most trials included in the analysis did not extend beyond 24 weeks, the risk of suicidal thoughts or behavior beyond 24 weeks could not be assessed. The risk of suicidal thoughts or behavior was generally consistent among drugs in the data analyzed. The finding of increased risk with AEDs of varying mechanisms of action and across a range of indications suggests that the risk applies to all AEDs used for any indication. The risk did not vary substantially by age (5-100 years) in the clinical trials analyzed. Table 1 shows absolute and relative risk by indication for all evaluated AEDs.

Table 1. Risk by Indication for Antiepileptic Drugs in the Pooled Analysis
Indication | Placebo Patients with Events/1000 Patients | Drug Patients with Events per 1000 Patients | Relative Risk: Incidence of Drug Events in Drug Patients /Incidence in Placebo Patients | Risk Difference: Additional Drug Patients with Events per 1000 Patients
Epilepsy | 1.0 | 3.4 | 3.5 | 2.4
Psychiatric | 5.7 | 8.5 | 1.5 | 2.9
Other | 1.0 | 1.8 | 1.9 | 0.9
Total | 2.4 | 4.3 | 1.8 | 1.9

The relative risk for suicidal thoughts or behavior was higher in clinical trials for epilepsy than in clinical trials for psychiatric or other conditions, but the absolute risk differences were similar for the epilepsy and psychiatric indications.

Anyone considering prescribing midazolam or any other AED must balance the risk of suicidal thoughts or behaviors with the risk of untreated illness. Epilepsy and many other illnesses for which AEDs are prescribed are themselves associated with morbidity and mortality and an increased risk of suicidal thoughts and behavior. Should suicidal thoughts and behavior emerge during treatment, the prescriber needs to consider whether the emergence of these symptoms in any given patient may be related to the illness being treated.

5.7 Impaired Cognitive Function

Midazolam, including NAYZILAM, is associated with a high incidence of partial or complete impairment of recall for several hours following an administered dose. Gross tests of recovery from the effects of midazolam cannot be relied upon to predict reaction time under stress. It is recommended that no patient operate hazardous machinery or a motor vehicle until the effects of the drug, such as drowsiness, have subsided, and as their medical condition permits. For pediatric patients, particular care should be taken to ensure safe ambulation.

5.8 Glaucoma

Benzodiazepines, including NAYZILAM, can increase intraocular pressure in patients with glaucoma. Measurements of intraocular pressure in patients without eye disease show a moderate lowering following induction with midazolam. NAYZILAM may be used in patients with open-angle glaucoma only if they are receiving appropriate therapy. Patients with open-angle glaucoma may need to have their ophthalmologic status evaluated following treatment with NAYZILAM. NAYZILAM is contraindicated in patients with narrow-angle glaucoma.

5.9 Neonatal Sedation and Withdrawal Syndrome

Use of NAYZILAM late in pregnancy can result in sedation (respiratory depression, lethargy, hypotonia) and/or withdrawal symptoms (hyperreflexia, irritability, restlessness, tremors, inconsolable crying, and feeding difficulties) in the neonate [see Use in Specific Populations (8.1)]. Monitor neonates exposed to NAYZILAM during pregnancy or labor for signs of sedation and monitor neonates exposed to NAYZILAM during pregnancy for signs of withdrawal; manage these neonates accordingly.

5.10 Other Adverse Reactions

When midazolam was used for sedation, reactions such as agitation, involuntary movements (including tonic/clonic movements and muscle tremor), hyperactivity, and combativeness have been reported. These reactions may be caused by inadequate or excessive dosing or improper administration of midazolam; however, consideration should be given to the possibility of cerebral hypoxia or true paradoxical reactions.

6 ADVERSE REACTIONS

The following serious adverse reactions are discussed in more detail in other sections of the labeling:

- Risks from Concomitant Use with Opioids [see Warnings and Precautions (5.1)]
- Abuse, Misuse, and Addiction [see Warnings and Precautions (5.2)]
- Dependence and Withdrawal Reactions After Use of NAYZILAM More Frequently Than Recommended [see Warnings and Precautions (5.3)]
- Risks of Cardiorespiratory Adverse Reactions [see Warnings and Precautions (5.4)]
- CNS Depression from Concomitant Use with Other CNS Depressants or Moderate or Strong CYP3A4 Inhibitors [see Warnings and Precautions (5.5)]
- Suicidal Behavior and Ideation [see Warnings and Precautions (5.6)]
- Impaired Cognitive Function [see Warnings and Precautions (5.7)]
- Glaucoma [see Warnings and Precautions (5.8)]
- Neonatal Sedation and Withdrawal Syndrome [see Warnings and Precautions (5.9)]
- Other Adverse Reactions [see Warnings and Precautions (5.10)]

6.1 Clinical Trials Experience

Because clinical trials are conducted under widely varying conditions, adverse reaction rates observed in the clinical trials of a drug cannot be directly compared to rates in the clinical trials of another drug and may not reflect the rates observed in clinical practice.

NAYZILAM was studied for the outpatient treatment of a single seizure cluster in 292 adult and adolescent patients with epilepsy (Study 1) [see Clinical Studies (14)]. The study was conducted in two phases; an open-label Test Dose Phase followed by a double-blind, placebo-controlled, Comparative Phase. The mean age of patients enrolled in the Comparative Phase (N=201) was 33 years, 51% were female, and 95% were White.

Table 2 lists the adverse reactions occurring in 2% or more of the NAYZILAM-treated patients and at a rate greater than the placebo-treated patients in the Comparative Phase of Study 1.

Table 2: Adverse Reactions [Adverse reactions that occurred within 2 days after NAYZILAM administration are included] that Occurred in ≥2% of Patients (Any NAYZILAM) and Greater than Placebo in the Comparative Phase of Study 1
Body System/Adverse Reaction | Placebo | NAYZILAM [Patients in Study 1 were permitted to take a second, open-label dose of NAYZILAM 5 mg between 10 minutes and 6 hours following the initial blinded dose of NAYZILAM 5 mg or placebo if they experience seizure recurrence or an incomplete resolution of the episode. The Placebo + NAYZILAM 5 mg and NAYZILAM 5 mg + 5 mg columns represent patients who received a second dose of NAYZILAM 5 mg and received a blinded initial dose of placebo or NAYZILAM 5 mg, respectively.]
Body System/Adverse Reaction | Placebo | NAYZILAM 5 mg | Placebo + NAYZILAM 5 mg | NAYZILAM 5 mg + 5 mg | Any NAYZILAM Treatment Group
 | N = 26 % | N = 91 % | N = 41 % | N = 43 % | N = 175 %
Nervous System
Somnolence | 4 | 10 | 10 | 9 | 10
Headache | 0 | 7 | 0 | 2 | 4
Dysarthria | 0 | 2 | 2 | 2 | 2
Application Site
Nasal Discomfort | 8 | 5 | 7 | 16 | 9
Throat Irritation | 0 | 2 | 2 | 7 | 3
Rhinorrhea | 0 | 3 | 0 | 5 | 3
Product Taste Abnormal | 0 | 4 | 0 | 0 | 2
Eye Disorders
Lacrimation Increased | 0 | 1 | 2 | 2 | 2

For patients who experienced a decrease in peripheral oxygen saturation in the Test Dose Phase of Study 1, the decreases were generally transitory. Two patients (one with a history of sleep apnea and one with intercurrent seizure) with decreases in peripheral oxygen saturation in the Test Dose Phase required therapeutic supplemental oxygen.

7 DRUG INTERACTIONS

Table 3: Clinically Significant Drug Interactions With NAYZILAM
7.1 CYP3A4 Inhibitors
Clinical Impact: | Concomitant use of CYP3A4 inhibitors may result in prolonged sedation because of a decrease in plasma clearance of midazolam.
Intervention: | Avoid co-administration of NAYZILAM with moderate or strong CYP3A4 inhibitors. NAYZILAM should be used with caution when co-administered with mild CYP3A4 inhibitors.
Examples: | Moderate CYP3A4 inhibitors: erythromycin, diltiazem, verapamil Strong CYP3A4 inhibitors: ketoconazole, itraconazole, clarithromycin
7.2 Opioids
Clinical Impact: | The concomitant use of benzodiazepines and opioids increases the risk of respiratory depression because of actions at different receptor sites in the CNS that control respiration. Benzodiazepines interact at GABAA sites and opioids interact primarily at mu receptors. When benzodiazepines and opioids are combined, the potential for benzodiazepines to significantly worsen opioid-related respiratory depression exists.
Intervention: | Reserve concomitant prescribing of these drugs for use in patients for whom alternative treatment options are inadequate. Limit dosages and durations to the minimum required [see Warnings and Precautions (5.1)].
Examples: | Morphine, hydrocodone, oxymorphone, codeine, fentanyl
7.3 Other Central Nervous System (CNS) Depressants
Clinical Impact: | Concomitant use of barbiturates, alcohol, or other CNS depressants may increase the risk of hypoventilation, airway obstruction, desaturation, or apnea and may contribute to profound and/or prolonged drug effect.
Intervention: | Reserve concomitant prescribing of these drugs for use in patients for whom alternative treatment options are inadequate. Limit dosages and durations to the minimum required [see Warnings and Precautions (5.5)].
Examples: | Other benzodiazepines and sedatives/hypnotics, anxiolytics, tranquilizers, muscle relaxants, general anesthetics, antipsychotics, opioids, alcohol.

8 USE IN SPECIFIC POPULATIONS

8.1 Pregnancy

Pregnancy Exposure Registry

There is a pregnancy exposure registry that monitors pregnancy outcomes in women exposed to antiepileptic drugs (AEDs), such as NAYZILAM, during pregnancy. Healthcare providers are encouraged to recommend that pregnant women who are taking NAYZILAM during pregnancy enroll in the North American Antiepileptic Drug (NAAED) pregnancy registry by calling 1-888-233-2334 or visiting http://www.aedpregnancyregistry.org/.

Risk Summary

Neonates born to mothers using benzodiazepines late in pregnancy have been reported to experience symptoms of sedation and/or neonatal withdrawal [see Warnings and Precautions (5.9) and Clinical Considerations]. Available data from published observational studies of pregnant women exposed to benzodiazepines do not report a clear association with benzodiazepines and major birth defects (see Data).

Administration of midazolam to rats and rabbits during the period of organogenesis or to rats during late pregnancy and throughout lactation at doses greater than those used clinically did not result in any apparent adverse effects on development (see Animal Data). However, published data for midazolam and other benzodiazepines suggest the possibility of neuronal cell death and long-term effects on neurobehavioral and immunological function in animals following prenatal or early postnatal exposure at clinically relevant doses.

The background risk of major birth defects and miscarriage for the indicated population is unknown. All pregnancies have a background risk of birth defect, loss, or other adverse outcomes. In the U.S. general population, the estimated background risk of major birth defects and miscarriage in clinically recognized pregnancies is 2 to 4% and 15 to 20%, respectively.

Clinical Considerations

Fetal/Neonatal Adverse Reactions

Benzodiazepines cross the placenta and may produce respiratory depression, hypotonia, and sedation in neonates. Monitor neonates exposed to NAYZILAM during pregnancy or labor for signs of sedation, respiratory depression, hypotonia, and feeding problems. Monitor neonates exposed to NAYZILAM during pregnancy for signs of withdrawal. Manage these neonates accordingly [see Warnings and Precautions (5.9)].

Data

Human Data

Published data from observational studies on the use of benzodiazepines during pregnancy do not report a clear association with benzodiazepines and major birth defects. Although early studies reported an increased risk of congenital malformations with diazepam and chlordiazepoxide, there was no consistent pattern noted. In addition, the majority of more recent case-control and cohort studies of benzodiazepine use during pregnancy, which were adjusted for confounding exposures to alcohol, tobacco and other medications, have not confirmed these findings.

Animal Data

When midazolam (0, 0.2, 1, or 4 mg/kg/day) was administered intravenously to pregnant rats during the period of organogenesis, no adverse effects on embryofetal development were observed. The highest dose tested, which was associated with minimal evidence of maternal toxicity, is approximately 4 times the maximum recommended human dose (MRHD) of 10 mg based on body surface area (mg/m^2).

When midazolam (0, 0.2, 0.6, and 2 mg/kg/day) was administered intravenously to rabbits during the period of organogenesis, no adverse effects on embryofetal development were reported. The high dose, which was not associated with evidence of maternal toxicity, is approximately 4 times the MRHD on a mg/m^2 basis.

When midazolam (0, 0.2, 1, or 4 mg/kg/day) was administered intravenously to female rats during late gestation and throughout lactation, no clear adverse effects were noted in the offspring. The high dose, which was not associated with evidence of maternal toxicity, is approximately 4 times the MRHD on a mg/m^2 basis.

In published animal studies, administration of benzodiazepines, including midazolam, or other drugs that enhance GABAergic neurotransmission to neonatal rats has been reported to result in widespread apoptotic neurodegeneration in the developing brain at plasma concentrations relevant for seizure control in humans. The window of vulnerability to these changes in rats (postnatal days 0-14) includes a period of brain development corresponding to that taking place during the third trimester of pregnancy in humans.

8.2 Lactation

Risk Summary

Midazolam is excreted in human milk. There are reports of sedation, poor feeding and poor weight gain in infants exposed to benzodiazepines through breast milk. There are no data on the effects of midazolam on milk production.

The developmental and health benefits of breastfeeding should be considered along with the mother's clinical need for NAYZILAM and any potential adverse effects on the breastfed infant from NAYZILAM or from the underlying maternal condition.

Clinical Considerations

Infants exposed to NAYZILAM through breast milk should be monitored for sedation, poor feeding and poor weight gain.

8.4 Pediatric Use

Safety and effectiveness of NAYZILAM have been evaluated in the age group 12 to 17 years. Use of NAYZILAM in this age group is supported by evidence from an adequate and well-controlled study of NAYZILAM in adults and adolescents with seizure clusters [see Clinical Studies (14)] and pharmacokinetic and safety data from adult and pediatric patients [see Clinical Pharmacology (12.3)].

Safety and effectiveness in pediatric patients below the age of 12 years have not been established.

8.5 Geriatric Use

Safety and efficacy studies of NAYZILAM did not include sufficient numbers of subjects aged 65 and over to determine whether they respond differently from younger subjects. Geriatric patients have longer elimination half-lives for midazolam and its metabolites, which may result in prolonged drug exposure. Geriatric patients may have altered drug distribution; diminished hepatic and/or renal function; and subjects over 70 years of age may be particularly sensitive [see Clinical Pharmacology (12.3)]. Administration of intramuscular (IM) midazolam to elderly patients has been associated with rare reports of death under circumstances compatible with cardiorespiratory depression [see Warnings and Precautions (5.4)]. In most of these cases, the patients also received other CNS depressants capable of depressing respiration, especially narcotics [see Warnings and Precautions (5.1, 5.5)]. Close monitoring of geriatric patients is recommended.

8.6 Renal Impairment

Based on a population pharmacokinetic analysis of patients administered NAYZILAM, midazolam and 1-OH midazolam pharmacokinetics are expected to be similar in subjects with mild renal impairment when compared to normal subjects. Safety and efficacy studies of NAYZILAM did not include patients with severe renal impairment and there were not enough subjects with moderate renal impairment in clinical studies for population pharmacokinetic analysis. Patients with moderate and severe renal impairment may have slower elimination of midazolam and its metabolites, which may result in prolonged drug exposure [see Clinical Pharmacology (12.3)].

8.7 Congestive Heart Failure

Patients with congestive heart failure eliminate midazolam more slowly, which may result in prolonged drug exposure [see Clinical Pharmacology (12.3)].

9 DRUG ABUSE AND DEPENDENCE

9.1 Controlled Substance

NAYZILAM contains midazolam, a Schedule IV controlled substance.

9.2 Abuse

NAYZILAM is a benzodiazepine and a CNS depressant with a potential for abuse and addiction. Abuse is the intentional, non-therapeutic use of a drug, even once, for its desirable psychological or physiological effects. Misuse is the intentional use, for therapeutic purposes, of a drug by an individual in a way other than prescribed by a health care provider or for whom it was not prescribed. Drug addiction is a cluster of behavioral, cognitive, and physiological phenomena that may include a strong desire to take the drug, difficulties in controlling drug use (e.g., continuing drug use despite harmful consequences, giving a higher priority to drug use than other activities and obligations), and possible tolerance or physical dependence. Even taking benzodiazepines as prescribed may put patients at risk for abuse and misuse of their medication. Abuse and misuse of benzodiazepines may lead to addiction.

Abuse and misuse of benzodiazepines often (but not always) involve the use of doses greater than the maximum recommended dosage and commonly involve concomitant use of other medications, alcohol, and/or illicit substances, which is associated with an increased frequency of serious adverse outcomes, including respiratory depression, overdose, or death. Benzodiazepines are often sought by individuals who abuse drugs and other substances, and by individuals with addictive disorders [see Warnings and Precautions (5.2)].

The following adverse reactions have occurred with benzodiazepine abuse and/or misuse: abdominal pain, amnesia, anorexia, anxiety, aggression, ataxia, blurred vision, confusion, depression, disinhibition, disorientation, dizziness, euphoria, impaired concentration and memory, indigestion, irritability, muscle pain, slurred speech, tremors, and vertigo.

The following severe adverse reactions have occurred with benzodiazepine abuse and/or misuse: delirium, paranoia, suicidal ideation and behavior, seizures, coma, breathing difficulty, and death. Death is more often associated with polysubstance use (especially benzodiazepines with other CNS depressants such as opioids and alcohol).

Midazolam was actively self-administered in primate models used to assess the positive reinforcing effects of psychoactive drugs. Midazolam produced physical dependence of a mild to moderate intensity in cynomolgus monkeys after 5 to 10 weeks of administration.

Assessment of the abuse-related subjective effects comparing NAYZILAM to oral midazolam syrup was conducted in adult subjects with a history of benzodiazepine recreational drug use. No statistically significant or clinically-relevant differences in subjective positive effects (i.e., Drug Liking, Overall Drug Liking, Take Drug Again, and High) were observed between NAYZILAM and oral midazolam syrup. However, subjective positive effects on all these measures were significantly greater for NAYZILAM than for placebo confirming that NAYZILAM has abuse potential. Somnolence occurred at a similar rate in both midazolam groups, but euphoric mood occurred at a greater rate in NAYZILAM (4 to 16%) compared to the oral midazolam syrup (4 to 8.5%).

9.3 Dependence

Physical Dependence After Use of NAYZILAM More Frequently Than Recommended

NAYZILAM may produce physical dependence if used more frequently than recommended. Physical dependence is a state that develops as a result of physiological adaptation in response to repeated drug use, manifested by withdrawal signs and symptoms after abrupt discontinuation or a significant dose reduction of a drug. Although NAYZILAM is indicated only for intermittent use [see Indications and Usage (1) and Dosage and Administration (2)], if used more frequently than recommended, abrupt discontinuation or rapid dosage reduction or administration of flumazenil, a benzodiazepine antagonist, may precipitate acute withdrawal reactions, including seizures, which can be life-threatening. Patients at an increased risk of withdrawal adverse reactions after benzodiazepine discontinuation or rapid dosage reduction include those who take higher dosages (i.e., higher and/or more frequent doses) and those who have had longer durations of use [see Warnings and Precautions (5.3)]. For patients using NAYZILAM more frequently than recommended, to reduce the risk of withdrawal reactions, use a gradual taper to discontinue NAYZILAM [see Warnings and Precautions (5.3)].

Acute Withdrawal Signs and Symptoms

Acute withdrawal signs and symptoms associated with benzodiazepines have included abnormal involuntary movements, anxiety, blurred vision, depersonalization, depression, derealization, dizziness, fatigue, gastrointestinal adverse reactions (e.g., nausea, vomiting, diarrhea, weight loss, decreased appetite), headache, hyperacusis, hypertension, irritability, insomnia, memory impairment, muscle pain and stiffness, panic attacks, photophobia, restlessness, tachycardia, and tremor. More severe acute withdrawal signs and symptoms, including life-threatening reactions, have included catatonia, convulsions, delirium tremens, depression, hallucinations, mania, psychosis, seizures, and suicidality.

Protracted Withdrawal Syndrome

Protracted withdrawal syndrome associated with benzodiazepines is characterized by anxiety, cognitive impairment, depression, insomnia, formication, motor symptoms (e.g., weakness, tremor, muscle twitches), paresthesia, and tinnitus that persists beyond 4 to 6 weeks after initial benzodiazepine withdrawal. Protracted withdrawal symptoms may last weeks to more than 12 months. As a result, there may be difficulty in differentiating withdrawal symptoms from potential re-emergence or continuation of symptoms for which the benzodiazepine was being used.

Tolerance

Tolerance to NAYZILAM may develop after use more frequently than recommended. Tolerance is a physiological state characterized by a reduced response to a drug after repeated administration (i.e., a higher dose of a drug is required to produce the same effect that was once obtained at a lower dose).

Tolerance to the therapeutic effect of benzodiazepines may develop; however, little tolerance develops to the amnestic reactions and other cognitive impairments caused by benzodiazepines.

9.4 Chronic Use

NAYZILAM is not recommended for chronic, daily use as an anticonvulsant because of the potential for development of tolerance to midazolam. In clinical trials, patients were treated with NAYZILAM no more frequently than every 3 days.

Chronic daily use of benzodiazepines may increase the frequency and/or severity of tonic-clonic seizures, requiring an increase in the dosage of standard anticonvulsant medication. In such cases, abrupt withdrawal of chronic benzodiazepines may also be associated with a temporary increase in the frequency and/or severity of seizures.

10 OVERDOSAGE

Overdosage of benzodiazepines is characterized by central nervous system depression ranging from drowsiness to coma. In mild to moderate cases, symptoms can include drowsiness, confusion, dysarthria, lethargy, hypnotic state, diminished reflexes, ataxia, and hypotonia. Rarely, paradoxical or disinhibitory reactions (including agitation, irritability, impulsivity, violent behavior, confusion, restlessness, excitement, and talkativeness) may occur. In severe overdosage cases, patients may develop respiratory depression and coma. Overdosage of benzodiazepines in combination with other CNS depressants (including alcohol and opioids) may be fatal [see Warnings and Precautions (5.2)]. Markedly abnormal (lowered or elevated) blood pressure, heart rate, or respiratory rate raise the concern that additional drugs and/or alcohol are involved in the overdosage.

In managing benzodiazepine overdosage, employ general supportive measures, including intravenous fluids and airway maintenance. Flumazenil, a specific benzodiazepine receptor antagonist indicated for the complete or partial reversal of the sedative effects of benzodiazepines in the management of benzodiazepine overdosage, can lead to withdrawal and adverse reactions, including seizures, particularly in the context of mixed overdosage with drugs that increase seizure risk (e.g., tricyclic and tetracyclic antidepressants) and in patients with long-term benzodiazepine use and physical dependency. The risk of withdrawal seizures with flumazenil may be increased in patients with epilepsy. Flumazenil is contraindicated in patients who have received a benzodiazepine for control of a potentially life-threatening condition (e.g., status epilepticus). If the decision is made to use flumazenil, it should be used as an adjunct to, not as a substitute for, supportive management of benzodiazepine overdosage. See the flumazenil injection Prescribing Information.

Consider contacting the Poison Help line (1-800-222-1222) or medical toxicologist for additional overdosage management recommendations.

11 DESCRIPTION

NAYZILAM contains midazolam, a compound of the benzodiazepine class. Midazolam is chemically designated as 8-Chloro-6-(ο-fluorophenyl)-1-methyl-4H-imidazo[1,5-a][1,4]benzodiazepine, and it has the following structure:

The empirical formula is C18H13ClFN3 representing a molecular weight of 325.8. Midazolam, USP is a white or yellowish, crystalline powder that is practically insoluble in water, soluble in methanol, and freely soluble in acetone and in alcohol.

NAYZILAM nasal spray is a clear, colorless to yellowish colored liquid. Each single-dose NAYZILAM unit is for nasal administration and delivers 5 mg of midazolam in 0.1 mL of solution containing ethanol; PEG-6 methyl ether; polyethylene glycol 400; propylene glycol; and purified water.

The pH range of solution is approximately 5.0 to 9.0.

12 CLINICAL PHARMACOLOGY

12.1 Mechanism of Action

The exact mechanism of action for midazolam is not fully understood, but it is thought to involve potentiation of GABAergic neurotransmission resulting from binding at the benzodiazepine site of the GABAA receptor.

12.2 Pharmacodynamics

The pharmacodynamic properties of midazolam and its metabolites, are similar to those of other benzodiazepines, including sedative, anxiolytic, amnestic, and hypnotic activities. The effects of midazolam on the CNS are dependent on the dose administered, the route of administration, and the presence or absence of other medications.

Treatment with NAYZILAM was associated with effects on measures of sedation and measures of psychomotor performance [see Warnings and Precautions (5.5)]. Sedation and psychomotor impairment effects generally began to occur within 10 minutes post dose with peak effects observed within 30 minutes to 2 hours post dose. The pharmacodynamic effects generally returned to near baseline levels by 4 hours post-dose.

12.3 Pharmacokinetics

Pharmacokinetics

Based on a population pharmacokinetic analysis, plasma exposures (Cmax and AUC) of midazolam in epilepsy patients increase approximately proportional to dose from 5.0 mg to 15 mg, 0.5 and 1.5 times the recommended maximum total dose (5 mg Initial Dose + 5 mg Second Dose), respectively.

Absorption

Following nasal administration of a single 5 mg midazolam dose to healthy adults, midazolam was absorbed with median Tmax (range) of 17.3 (7.8 to 28.2) minutes; midazolam mean (±SD) Cmax and AUC0-∞ were 54.7 (±30.4) ng/mL and 126.2 (±59) ng∙hr/mL, respectively. The mean absolute bioavailability is approximately 44%.

Distribution

In adults and pediatric patients, midazolam is approximately 97% bound to plasma protein, principally albumin. In healthy volunteers, 1-hydroxy midazolam is bound to the extent of 89%.

The estimated total volume of distribution of midazolam is 226.5 L.

In humans, midazolam has been shown to cross the placenta and enter into fetal circulation and has been detected in human milk and CSF [see Use in Specific Populations (8.1, 8.2)].

Elimination

Following administration of NAYZILAM in clinical trials, median midazolam and 1-hydroxy-midazolam elimination half-lives ranged from 2.1 to 6.2 hours and 2.7 to 7.2 hours, respectively, independent of dose.

Metabolism

Midazolam is primarily metabolized by liver and intestinal cytochrome P450 3A4 (CYP3A4) to its pharmacologic active metabolite, 1-hydroxy midazolam (also termed α-hydroxy-midazolam). Midazolam is also metabolized to two other minor metabolites: 4-hydroxy metabolite and 1,4-dihydroxy metabolite. The principal urinary excretion products are glucuronide conjugates of the hydroxylated derivatives.

Studies of the intravenous administration of 1-hydroxy-midazolam in humans suggest that 1-hydroxy-midazolam is at least as potent as the parent compound and may contribute to the net pharmacologic activity of midazolam.

Excretion

The principal urinary excretion product is 1-OH midazolam in the form of a glucuronide conjugate. Smaller amounts of the glucuronide conjugates of 4-hydroxy- and dihydroxy-midazolam are detected as well.

Specific Populations

Geriatric Patients

In a parallel group study of 2.5 mg and 5 mg doses of NAYZILAM, mean systemic exposure (AUC) and peak plasma concentrations (Cmax) of midazolam were 21 to 45% higher in geriatric subjects (> 65 years old) as compared to non-geriatric subjects. The terminal half-life was increased by approximately 2 hours in the geriatric subjects because of a decrease in clearance [see Use in Specific Populations (8.5)].

Obesity

In a study comparing normal (n=20) and obese patients (n=20), the mean half-life of midazolam administered by parental route was greater in the obese group (5.9 versus 2.3 hours). This was because of an increase of approximately 50% in the volume of distribution (Vd) corrected for total body weight. The clearance was not significantly different between groups.

Patients with Renal Impairment

Patients with renal impairment may have longer elimination half-lives for midazolam and its metabolites [see Use in Specific Populations (8.6)].

Midazolam and 1-hydroxy-midazolam pharmacokinetics in 6 ICU patients who developed acute renal failure (ARF) were compared with a normal renal function control group. Midazolam was administered as an infusion (5 to 15 mg/hr). Midazolam clearance was reduced (1.9 vs 2.8 mL/min/kg) and the half-life was prolonged (7.6 vs 13 hours) in the ARF patients. The renal clearance of the 1-hydroxy-midazolam glucuronide was prolonged in the ARF group (4 vs 136 mL/min) and the half-life was prolonged (12 vs >25 hours). Plasma levels accumulated in all ARF patients to about ten times that of the parent drug. The relationship between accumulating metabolite levels and prolonged sedation is unclear.

In a study of chronic renal failure patients (n=15) receiving a single intravenous dose of midazolam, there was a 2-fold increase in the clearance and volume of distribution, but the half-life remained unchanged.

Patients with Hepatic Impairment

Midazolam pharmacokinetics were studied after an intravenous single dose (0.075 mg/kg) was administered to patients with biopsy proven alcoholic cirrhosis (n=7) and control patients (n=8). The mean half-life of midazolam increased 2.5-fold in the patients with cirrhosis. Clearance was reduced by 50% and the Vd increased by 20%. In another study in male patients with cirrhosis (n=21) without ascites and with normal kidney function as determined by creatinine clearance, no changes in the pharmacokinetics of midazolam or 1-hydroxy-midazolam were observed when compared to healthy individuals. The clinical significance of these findings is unknown.

Patients with Congestive Heart Failure

In patients suffering from congestive heart failure, a 2-fold increase in the elimination half-life, a 25% decrease in the plasma clearance, and a 40% increase in the volume of distribution of midazolam were observed.

Drug Interaction Studies

Since NAYZILAM is metabolized by CYP3A4, interactions with drugs that inhibit or induce CYP3A4 are likely.

Inhibitors of CYP3A4 Isozymes

Coadministration of CYP3A4 inhibitors with NAYZILAM has not been studied. However, the effects of inhibitors on midazolam exposure following NAYZILAM administration are expected to be similar to those following IV midazolam administration. Concomitant use of CYP3A4 inhibitors may result in prolonged sedation because of a decrease in plasma clearance of midazolam [Warnings and Precautions (5.5) and Drug Interactions (7.1)].

- The effect of single oral doses of 800 mg cimetidine and 300 mg ranitidine on steady-state concentrations of oral midazolam was examined in a randomized crossover study (n=8). Cimetidine increased the mean midazolam steady-state concentration from 57 to 71 ng/mL. Ranitidine increased the mean steady-state concentration to 62 ng/mL. No change in choice reaction time or sedation index was detected after dosing with the H2 receptor antagonists.
- In a placebo-controlled study, erythromycin administered as a 500 mg dose, three times a day, for 1 week (n=6), reduced the clearance of midazolam following a single 0.5 mg/kg IV dose. The half-life was approximately doubled.
- The effects of diltiazem (60 mg three times a day) and verapamil (80 mg three times a day) on the pharmacokinetics and pharmacodynamics of midazolam were investigated in a three-way crossover study (n=9). The half-life of midazolam increased from 5 to 7 hours when midazolam was taken in conjunction with verapamil or diltiazem. No interaction was observed in healthy subjects between midazolam and nifedipine.
- In a placebo-controlled study, where saquinavir or placebo was administered orally as a 1200 mg dose three times a day for 5 days (n=12), a 56% reduction in the clearance of midazolam following a single 0.05 mg/kg IV dose was observed. The half-life was approximately doubled.

Inducers of CYP3A4 Isozymes

Exposures (e.g., combined Cmax or AUC of midazolam and the 1-OH-midazolam active metabolite) are decreased 16 to 26% when NAYZILAM is co-administered with anti-epileptic drugs that are strong CYP3A4 inducers (e.g., phenytoin, phenobarbital, primidone, carbamazepine). Exposures (e.g., combined Cmax or AUC of midazolam and the 1-OH-midazolam active metabolite) are decreased 8 to 15% when NAYZILAM is co-administered with anti-epileptic drugs that are weak to moderate CYP3A4 inducers (e.g., clobazam, eslicarbazepine, felbamate, oxcarbazepine, rufinamide, topiramate). These changes in exposures are not expected to be clinically significant.

13 NONCLINICAL TOXICOLOGY

13.1 Carcinogenesis, Mutagenesis, Impairment of Fertility

Carcinogenesis

Midazolam maleate was administered in the diet to mice and rats for 2 years at doses of 0, 1, 9, or 80 mg/kg/day. In female mice in the highest dose group there was a marked increase in the incidence of hepatic tumors. In high-dose male rats there was a small but statistically significant increase in benign thyroid follicular cell tumors. The highest dose not associated with increased tumor incidences in mice and rats (9 mg/kg/day) is approximately 4 and 9 times, respectively, the recommended human dose (RHD) of 10 mg based on body surface area (mg/m^2). The pathogenesis of induction of these tumors is not known. These tumors were found after chronic administration, whereas human use will ordinarily be of single or several doses.

Mutagenesis

Midazolam was negative for genotoxicity in in vitro (Ames, mammalian cell clastogenicity) and in vivo (mouse bone marrow micronucleus) assays.

Impairment of Fertility

When midazolam (0, 1, 4, or 16 mg/kg) was orally administered to male and female rats prior to and during mating and continuing in females throughout gestation and lactation, no adverse effects on male or female fertility were noted.

14 CLINICAL STUDIES

The effectiveness of NAYZILAM for the acute treatment of intermittent, stereotypic episodes of frequent seizure activity (i.e., seizure clusters, acute repetitive seizures) that are distinct from a patient's usual seizure pattern in patients with epilepsy 12 years of age and older was established in a randomized, double-blind, placebo-controlled trial (Study 1; NCT 01390220).

Study 1 enrolled patients with epilepsy on a stable regimen of antiepileptic drugs who were identified by their physicians as having intermittent, stereotypic episodes of frequent seizure activity that were distinct from the patient's usual seizure pattern.

Study 1 was conducted in two phases: an open-label Test Dose Phase followed by a randomized, double-blind, placebo-controlled, Comparative Phase. In the Test Dose Phase, tolerability was assessed in 292 patients who, in the absence of a seizure, received two 5 mg doses of NAYZILAM (10 mg total dosage) separated by 10 minutes. Patients were excluded from participation in the Comparative Phase if they failed to meet pre-defined blood pressure, heart rate, sedation, electrocardiogram, and peripheral oxygen saturation criteria.

In the Comparative Phase, 201 patients treated a single seizure cluster episode in an outpatient setting with either a blinded dose of NAYZILAM 5 mg (134 patients) or placebo (67 patients). If the seizure activity persisted or recurred, patients in both groups had the option to receive a subsequent unblinded dose of NAYZILAM 5 mg to be used between 10 minutes and 6 hours after administration of the initial blinded dose of study drug.

The primary efficacy endpoint for Study 1 was treatment success, defined as the termination of seizures within 10 minutes after the initial blinded dose of study drug and the absence of a recurrence of seizures within 6 hours of the initial blinded dose of study drug. A statistically significantly higher percentage of NAYZILAM-treated patients met the primary efficacy endpoint, as shown in Table 4.

Table 4: Primary Endpoint Results: Treatment Success (Study 1)
 | NAYZILAM (N=134) | Placebo (N=67)
Treatment success (%) | 53.7 | 34.3
95% CI | (45.3, 62.2) | (23.0, 45.7)
p-value | 0.011

Numerical differences in favor of NAYZILAM were observed on each of the components of the treatment success responder definition; termination of seizure(s) within 10 minutes after initial dose of study drug (80.6 versus 70.1%) and the absence of seizure recurrence between 10 minutes and 6 hours after the initial dose of study drug (58.2 versus 37.3%).

Study 1 also evaluated the occurrence and time to next seizure after the initial blinded dose of study drug. A smaller proportion of NAYZILAM-treated patients experienced the next seizure within 24 hours after the initial blinded dose of study drug (37.3% versus 46.3%). NAYZILAM-treated patients experienced a statistically longer time-to-next-seizure than the placebo group (Figure 1).

FIGURE 1: Kaplan-Meier Analysis of Time-to-Next-Seizure (Study 1)

Analysis by gender revealed no substantial differences in treatment response. Informative subgroup analyses by age and race were not possible because of the small percentage of patients less than 18 years of age or 65 years of age or greater, and of non-White patients in the study.

16 HOW SUPPLIED / STORAGE AND HANDLING

16.1 How Supplied

NAYZILAM is supplied as a solution of midazolam. Each single-dose nasal spray unit delivers 5 mg of midazolam in 0.1 mL of solution.

NAYZILAM is supplied in boxes of 2 nasal spray units (NDC 50474-500-15), each contained within an individual blister pack.

16.2 Storage and Handling

Do not open the blister packaging until ready to use. Do not test or prime before use.

Do not use if the nasal spray unit appears damaged.

Store at controlled room temperature 20°C to 25°C (68°F to 77°F). Excursions permitted to 15°C to 30°C (59°F to 86°F).

17 PATIENT COUNSELING INFORMATION

Advise patients and caregivers to read the FDA-approved patient labeling (Medication Guide and Instructions for Use).

Risks from Concomitant Use with Opioids

Inform patients and caregivers that potentially fatal additive effects may occur if NAYZILAM is used with opioids and not to use NAYZILAM concomitantly with opioids unless supervised by a healthcare provider. If a decision is made to prescribe NAYZILAM concomitantly with opioids, instruct caregivers to follow patients closely for signs and symptoms of respiratory depression and sedation [see Warnings and Precautions (5.1)].

Abuse, Misuse, and Addiction

Inform patients that use of NAYZILAM more frequently than recommended, even at recommended dosages, exposes users to risks of abuse, misuse, and addiction, which can lead to overdose and death, especially when used in combination with other medications (e.g., opioid analgesics), alcohol, and/or illicit substances. Inform patients about the signs and symptoms of benzodiazepine abuse, misuse, and addiction; to seek medical help if they develop these signs and/or symptoms; and on the proper disposal of unused drug [see Warnings and Precautions (5.2) and Drug Abuse and Dependence (9.2)].

Withdrawal Reactions

Inform patients that use of NAYZILAM more frequently than recommended may lead to clinically significant physical dependence and that abrupt discontinuation or rapid dosage reduction of NAYZILAM may precipitate acute withdrawal reactions, which can be life-threatening. Inform patients that in some cases, patients taking benzodiazepines have developed a protracted withdrawal syndrome with withdrawal symptoms lasting weeks to more than 12 months [see Warnings and Precautions (5.3) and Drug Abuse and Dependence (9.3)].

Risks of Cardiorespiratory Adverse Reactions

Warn patients and caregivers about the risks of respiratory depression, cardiac and respiratory arrest [see Warnings and Precautions (5.4)].

Advise caregivers on the signs and symptoms of respiratory depression to look for, how long to observe patients after administering NAYZILAM, the circumstances under which a second dose should not be given, and the circumstances under which emergency medical care should be summoned [see Dosage and Administration (2.1)].

CNS Depression from Concomitant Use with Other CNS Depressants

Warn patients and caregivers that the use of NAYZILAM in combination with alcohol or other CNS depressant drugs may increase the risk of hypoventilation, airway obstruction, desaturation, or apnea and may contribute to profound and/or prolonged drug effect [see Warnings and Precautions (5.5)].

Caution patients against engaging in hazardous occupations requiring mental alertness, such as operating machinery, driving a motor vehicle or riding a bicycle until they have completely returned to their level of baseline functioning.

Suicidal Behavior and Ideation

Counsel patients, their caregivers, and families that AEDs, including NAYZILAM, may increase the risk of suicidal thoughts and behavior and that they should be alert for the emergence or worsening of the signs and symptoms of depression, any unusual changes in mood or behavior or the emergence of suicidal thoughts, behavior or thoughts about self-harm. Behaviors of concern should be reported immediately to healthcare providers [see Warnings and Precautions (5.6)].

Impaired Cognitive Function

Warn patients that midazolam, including NAYZILAM, is associated with a high incidence of partial or complete impairment of recall for the next several hours. Counsel patients on when they can engage in activities requiring complete mental alertness, operate hazardous machinery, or drive a motor vehicle after taking NAYZILAM [see Warnings and Precautions (5.7)].

Pregnancy

Advise pregnant females that the use of NAYZILAM late in pregnancy can result in sedation (respiratory depression, lethargy, hypotonia) and/or withdrawal symptoms (hyperreflexia, irritability, restlessness, tremors, inconsolable crying, and feeding difficulties) in newborns [see Warnings and Precautions (5.9) and Use in Specific Populations (8.1)]. Instruct patients to inform their healthcare provider if they are pregnant. Encourage patients to enroll in the North American Antiepileptic Drug (NAAED) Pregnancy Registry if they become pregnant. The registry is collecting information about the safety of antiepileptic drugs during pregnancy [see Use in Specific Populations (8.1)].

Lactation

Counsel patients that midazolam, the active ingredient in NAYZILAM, is excreted in breast milk. Instruct patients to inform their healthcare provider if they are breastfeeding or intend to breastfeed. Instruct breastfeeding patients who take NAYZILAM to monitor their infants for excessive sedation, poor feeding and poor weight gain, and to seek medical attention if they notice these signs [see Use in Specific Populations (8.2)].

Important Treatment Instructions

Instruct patients and caregivers on what is and is not an intermittent and stereotypic episode of increased seizure activity (i.e., seizure cluster) that is appropriate for treatment, and the timing of administration in relation to the onset of the episode.

Instruct patients and caregivers on what to observe following administration, and what would constitute an outcome requiring immediate medical attention.

Instruct patients and caregivers not to administer a second dose of NAYZILAM if they are concerned by the patient's breathing, the patient requires emergency rescue treatment with assisted breathing or intubation, or there is excessive sedation [see Dosage and Administration (2.1)].

Advise patients and caregivers on how frequently they can treat successive seizure cluster episodes over time.

Administration Information

Advise patients and caregivers to not open the blister packaging until ready to use. Instruct them to not test or prime before use and to not use if the nasal spray unit appears damaged.

Manufactured for:
UCB, Inc., Smyrna, GA 30080

NAYZILAM® is a registered trademark of the UCB Group of Companies.
©2022. All rights reserved.

MEDICATION GUIDE
NAYZILAM® (NAY-zil-am)
(midazolam) nasal spray, CIV

What is the most important information I should know about NAYZILAM?

- NAYZILAM is a benzodiazepine medicine. Taking benzodiazepines with opioid medicines, alcohol, or other central nervous system (CNS) depressants (including street drugs) can cause severe drowsiness, breathing problems (respiratory depression), coma, and death.
- Get emergency medical help right away if any of the following happens:
  - shallow or slowed breathing
  - breathing stops (which may lead to the heart stopping)
  - excessive sleepiness (sedation)
    Do not drive or operate heavy machinery until you know how taking NAYZILAM with opioids may affect you.
- Risk of abuse, misuse, and addiction. There is a risk of abuse, misuse, and addiction with benzodiazepines, including NAYZILAM, which can lead to overdose and serious side effects including coma and death.
  - Serious side effects including coma and death have happened in people who have abused or misused benzodiazepines, including midazolam (the active ingredient in NAYZILAM). These serious side effects may also include delirium, paranoia, suicidal thoughts or actions, seizures, and difficulty breathing. Call your healthcare provider or go to the nearest hospital emergency room right away if you have any of these serious side effects.
  - You can develop an addiction even if you use NAYZILAM as prescribed by your healthcare provider.
  - Use NAYZILAM exactly as your healthcare provider prescribed.
  - Do not share your NAYZILAM with other people.
  - Keep NAYZILAM in a safe place and away from children.
- Physical dependence and withdrawal reactions. Benzodiazepines, including NAYZILAM, can cause physical dependence and withdrawal reactions, especially if you use NAYZILAM daily. NAYZILAM is not intended for daily use.
  - Do not suddenly stop using NAYZILAM without talking to your healthcare provider. Stopping NAYZILAM suddenly can cause serious and life-threatening side effects, including, unusual movements, responses, or expressions, seizures, sudden and severe mental or nervous system changes, depression, seeing or hearing things that others do not see or hear, an extreme increase in activity or talking, losing touch with reality, and suicidal thoughts or actions. Call your healthcare provider or go to the nearest hospital emergency room right away if you have any of these symptoms.
  - Some people who suddenly stop benzodiazepines have symptoms that can last for several weeks to more than 12 months, including, anxiety, trouble remembering, learning, or concentrating, depression, problems sleeping, feeling like insects are crawling under your skin, weakness, shaking, muscle twitching, burning or prickling feeling in your hands, arms, legs or feet, and ringing in your ears.
  - Physical dependence is not the same as drug addiction. Your healthcare provider can tell you more about the differences between physical dependence and drug addiction.
  - Do not use more NAYZILAM than prescribed or use NAYZILAM more often than prescribed.
- NAYZILAM can make you sleepy or dizzy and can slow your thinking and motor skills.
  - Do not drive, operate heavy machinery, or do other dangerous activities until you know how NAYZILAM affects you.
  - Do not drink alcohol or take other drugs that may make you sleepy or dizzy while using NAYZILAM without first talking to your healthcare provider. When taken with alcohol or drugs that cause sleepiness or dizziness, NAYZILAM may make your sleepiness or dizziness worse.
- Like other antiepileptic medicines, NAYZILAM may cause suicidal thoughts or actions in a very small number of people, about 1 in 500. Call your healthcare provider right away if you have any of these symptoms, especially if they are new, worse, or worry you:

- thoughts about suicide or dying
- feeling agitated or restless
- acting aggressive, being angry, or violent
- attempts to commit suicide
- panic attacks
- acting on dangerous impulses
- new or worse depression

- trouble sleeping (insomnia)
- an extreme increase in activity and talking (mania)
- new or worse anxiety
- new or worse irritability
- other unusual changes in behavior or mood

How can I watch for early symptoms of suicidal thoughts or actions?

- Pay attention to any changes, especially sudden changes in mood, behaviors, thoughts, or feelings.
- Keep all follow-up visits with your healthcare provider as scheduled.

Call your healthcare provider between visits as needed, especially if you are worried about symptoms.
Suicidal thoughts or actions can be caused by things other than medicines. If you have suicidal thoughts or actions, your healthcare provider may check for other causes.

What is NAYZILAM?

- NAYZILAM is a prescription medicine used for the short-term treatment of seizure clusters (also known as "acute repetitive seizures") in people 12 years of age and older.
- NAYZILAM is a federally controlled substance (CIV) because it contains midazolam that can be abused or lead to dependence. Keep NAYZILAM in a safe place to prevent misuse and abuse. Selling or giving away NAYZILAM may harm others and is against the law. Tell your healthcare provider if you have ever abused or been dependent on alcohol, prescription drugs, or street drugs.
- It is not known if NAYZILAM is safe and effective in children under 12 years of age.

Do not use NAYZILAM if you:

- are allergic to midazolam.
- have an eye problem called acute narrow-angle glaucoma.

Before you use NAYZILAM, tell your healthcare provider about all your medical conditions, including if you:

- have a history of depression, mood problems or suicidal thoughts or behavior.
- have asthma, emphysema, bronchitis, chronic obstructive pulmonary disease, or other breathing problems.
- have kidney or liver problems.
- have congestive heart failure.
- have a history of drug or alcohol abuse.
- are pregnant or plan to become pregnant.
  - Taking NAYZILAM late in pregnancy may cause your baby to have symptoms of sedation (breathing problems, sluggishness, low muscle tone), and/or withdrawal symptoms (jitteriness, irritability, restlessness, shaking, excessive crying, feeding problems).
  - Tell your healthcare provider right away if you become pregnant or think you are pregnant during treatment with NAYZILAM.
  - If you become pregnant while using NAYZILAM, talk to your healthcare provider about registering with the North American Antiepileptic Drug (NAAED) Pregnancy Registry. You can register by calling 1-888-233-2334. For more information about the registry, go to http://www.aedpregnancyregistry.org. The purpose of this registry is to collect information about the safety of antiepileptic drugs during pregnancy.
- are breastfeeding or plan to breastfeed. Midazolam passes into your breast milk and may harm your baby.
  - Breastfeeding during treatment with NAYZILAM may cause your baby to have sleepiness, feeding problems, and decreased weight gain.
  - Talk to your healthcare provider about the best way to feed your baby while you take NAYZILAM.

Tell your healthcare provider about all the medicines you take, including prescription and over-the-counter medicines, vitamins and herbal supplements. Using NAYZILAM with certain other medicines can affect each other, causing side effects. Know the medicines you take. Keep a list of them and show it to your healthcare provider and pharmacist each time you get a new medicine. Ask your healthcare provider or pharmacist for a list of these medicines if you are not sure.

How should I use NAYZILAM?

- Use NAYZILAM in the nose only.
- Use NAYZILAM exactly as your healthcare provider tells you to use it and follow the Instructions for Use that comes with this Medication Guide.
- Your healthcare provider has prescribed NAYZILAM to treat a type of seizure called a "seizure cluster".
- If the seizure cluster is continuing 10 minutes after the first dose of NAYZILAM, a second dose of NAYZILAM may be used if you have been told to do so by your healthcare provider.
- If a second dose of NAYZILAM is used, give the second dose in the other nostril.
- Do not give more than 2 doses of NAYZILAM to treat a seizure cluster.
- If the seizures do not stop after NAYZILAM is used, get emergency medical help right away.
- Do not use NAYZILAM for more than 1 seizure cluster episode every 3 days. Do not use NAYZILAM for more than 5 seizure cluster episodes per month.
- If benzodiazepines are stopped after a person takes them daily, they can cause withdrawal symptoms. Stopping benzodiazepines suddenly can cause seizures that will not stop (status epilepticus), hearing or seeing things that are not there (hallucinations), shaking, nervousness, and stomach and muscle cramps. NAYZILAM is not intended to be used daily.
- If you use too much NAYZILAM, call your healthcare provider or go to the nearest emergency room right away.

What should I avoid while using NAYZILAM?
See "What is the most important information I should know about NAYZILAM?"

What are the possible side effects of NAYZILAM?
NAYZILAM may cause serious side effects, including:

- See "What is the most important information I should know about NAYZILAM?"
- Increase in eye pressure in people with acute narrow-angle glaucoma. See "Do not use NAYZILAM if you:"

The most common side effects of NAYZILAM include:

- sleepiness
- headache
- runny nose

- nasal discomfort
- throat irritation

These are not all the possible side effects of NAYZILAM. Call your doctor for medical advice about side effects. You may report side effects to FDA at 1-800-FDA-1088.

How should I store NAYZILAM?

- Store NAYZILAM at room temperature between 68°F to 77°F (20°C to 25°C).
- Keep NAYZILAM in the blister package until ready to use.

Keep NAYZILAM and all medicines out of the reach of children.

General information about the safe and effective use of NAYZILAM.
Medicines are sometimes prescribed for purposes other than those listed in a Medication Guide. Do not use NAYZILAM for a condition for which it was not prescribed. Do not give NAYZILAM to other people, even if they have the same symptoms that you have. It may harm them. You can ask your healthcare provider or pharmacist for information about NAYZILAM that is written for health professionals.

What are the ingredients in NAYZILAM?
Active ingredient: midazolam
Inactive ingredients: ethanol, PEG-6 methyl ether, polyethylene glycol 400, propylene glycol and purified water
Manufactured for UCB, Inc., Smyrna, GA 30080.
NAYZILAM® is a registered trademark of the UCB Group of Companies.
©2022. All rights reserved.
For more information, go to www.nayzilam.com or call 1-844-599-2273.

This Medication Guide has been approved by the U.S. Food and Drug Administration

Issued: 1/2023

Instructions for Use
NAYZILAM® (NAY-zil-am)
(midazolam) nasal spray, CIV

You and your family members or caregivers should read this Instructions for Use before you start using NAYZILAM nasal spray and each time you get a refill. There may be new information. This information does not take the place of talking to your healthcare provider about your medical condition or treatment. If you and your family members or caregivers have any questions about NAYZILAM, ask your healthcare provider or pharmacist.

Important: NAYZILAM is for use in the nose only.

- There is only 1 dose of NAYZILAM in the nasal spray unit.
- Do not try to test or prime the nasal spray unit before use. You will lose the dose.
- Do not open the blister packaging until ready to use.
- Do not use if the nasal spray unit appears damaged.
- Do not use past the expiration date printed on the blister packaging.
- Throw away (dispose of) the nasal spray unit after use.

How to use NAYZILAM nasal spray:
Step 1: Peel open the blister packaging

- When ready to use, open the blister packaging.
- Hold blister packaging in the palm of your hand.
- On the foil backing, find the "Peel Here" tab and pull down (see Figure 1).
- Remove the nasal spray unit carefully.

Step 2: Hold the nasal spray unit

- Hold the nasal spray unit with your thumb on the plunger and your middle and index fingers on each side of the nozzle (see Figure 2).
- Do not press the plunger yet. If you press the plunger now, you will lose the dose.

Step 3: Place the tip into 1 nostril

- Place the tip of the nozzle into 1 nostril until your fingers on either side of the nozzle touches the bottom of the nose (see Figure 3).

Step 4: Press the plunger

- Press the plunger firmly to deliver the dose of NAYZILAM nasal spray (see Figure 4).
- Make sure to firmly press the plunger using 1 motion.

The patient does not need to breathe deeply when you give them the medicine.

What to do after the NAYZILAM nasal spray has been used:
Remove the nozzle from the nostril after giving the dose.
Note: The plunger will remain inside the nasal spray unit after the dose is given.
Throw away (dispose of) the nasal spray unit and blister packaging in the trash.
What to do if a Second Dose is needed:
Important: If the seizure cluster is continuing 10 minutes after the first dose of NAYZILAM, a second dose of NAYZILAM may be used if you have been told to do so by your healthcare provider.
If you need to give a second dose of NAYZILAM, follow the instructions in this Instructions for Use using a new nasal spray unit in the other nostril. (Repeat Step 1 through Step 4)

Call for help if any of the following happens:
- Seizure or seizures continue after giving NAYZILAM to the person as instructed by the healthcare provider. | Local Emergency Number:________________________
- Seizure behavior in the person is different from other episodes. | Healthcare Provider's Number:_______________________
- You are alarmed by the number or severity of the seizure or seizures in the person. | Information for Emergency Responder
- You are alarmed by the color or breathing of the person. | Time of first NAYZILAM dose:________________
- You are alarmed by the color or breathing of the person. | Time of second NAYZILAM dose (if given):_________________________

Manufactured for UCB, Inc., Smyrna, GA 30080.
NAYZILAM® is a registered trademark of the UCB Group of Companies. ©2022. All rights reserved.
For more information, go to www.nayzilam.com or call 1-844-599-2273.
This Instructions for Use has been approved by the U.S. Food and Drug Administration
Issued: 1/2023

PRINCIPAL DISPLAY PANEL - 5 mg Vial Blister Pack Carton

NDC 50474-500-15
Rx only

Nayzilam® CIV
(midazolam) nasal spray
5 mg

FOR NASAL USE ONLY
2 Nasal Spray Units
(1 dose per unit)

DO NOT test or prime before use.